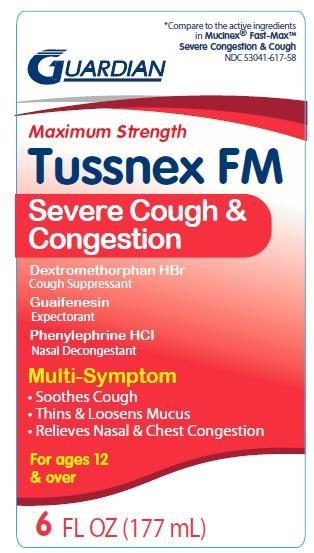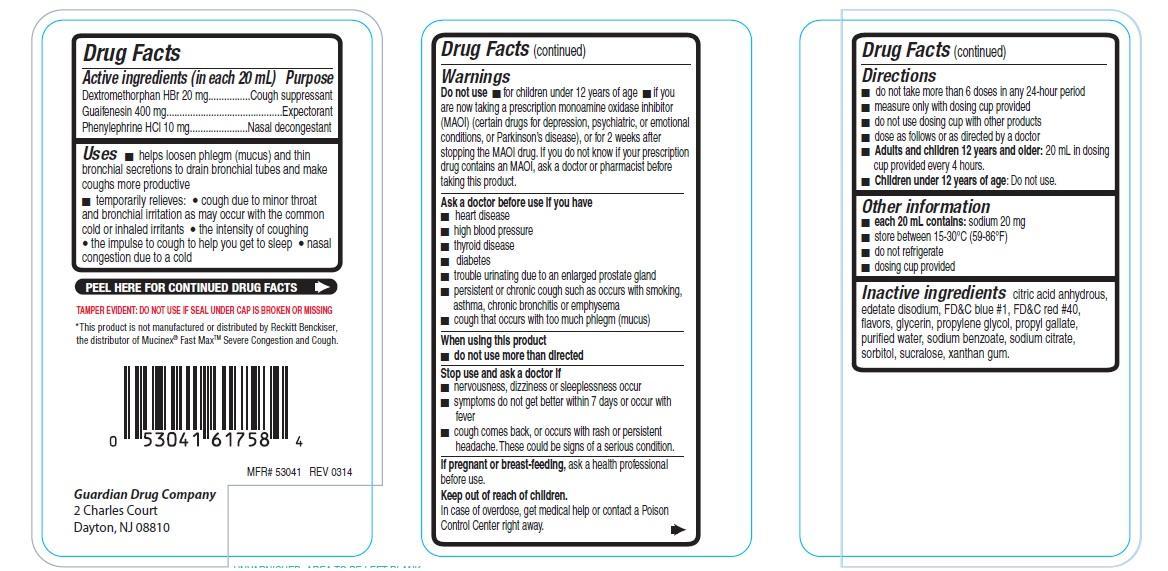 DRUG LABEL: Tussnex FM Severe cough and congestion
NDC: 53041-617 | Form: LIQUID
Manufacturer: Guardian Drug Company
Category: otc | Type: HUMAN OTC DRUG LABEL
Date: 20241219

ACTIVE INGREDIENTS: DEXTROMETHORPHAN HYDROBROMIDE 20 mg/20 mL; GUAIFENESIN 400 mg/20 mL; PHENYLEPHRINE HYDROCHLORIDE 10 mg/20 mL
INACTIVE INGREDIENTS: ANHYDROUS CITRIC ACID; EDETATE DISODIUM; FD&C BLUE NO. 1; FD&C RED NO. 40; GLYCERIN; PROPYLENE GLYCOL; PROPYL GALLATE; WATER; SODIUM BENZOATE; SODIUM CITRATE; SORBITOL; SUCRALOSE; XANTHAN GUM

Maximum strength Tussnex FM Severe cough and congestion

Active ingredients (in each 20 mL)

Dextromethorphan HBr 20 mg

Guaifenesin 400 mg

Phenylephrine HCl 10 mg

Purpose

Cough suppressant

Expectorant

Nasal decongestant

Uses

- hepls loosen phelgm (mucus) and thin bronchial secretions to drain bronchial tubes and make coughs more productive
- temporarily relieves:
- cough due to minor throat and bronchial irritation as may occur with the common cold or inhaled irritants
- the intensity of coughing
- the impulse to cough to help you get to sleep
- nasal congestion due to a cold

Warnings

Do not use

- for children under 12 years of age
- if you are now taking a prescription monoamine oxidase inhibitor (MAOI) (certain drugs for psychiatric, or emotional conditions, or Parkinson's disease), or for 2 weeks after stopping the MAOI drug. If you do not know if your prescription drug contains an MAOI, ask a doctor or pharmacist before taking this product.

Ask a doctor before use if you have

- heart disease
- high blood pressure
- thyroid disease
- diabetes
- trouble urinating due to an enlarged prostate gland
- persistent or chronic cough such as occurs with smoking, asthma, chronic bronchitis or emphysema
- cough that occurs with too much phlegm (mucus)

When using this product

- do not use more than directed

Stop use and ask a doctor if

- nervousness, dizziness or sleeplessness occur
- symptoms do not get better within 7 days or occur with fever
- cough comes back, or occurs with rash or persistent headache. These could be signs of a serious condition.

If pregnant or breast-feeding,

ask a health professional before use. Keep out of reach of children. In case of overdose, get medical help or contact a poison control center right away.

Directions

- do not take more than 6 doses in 24-hour period
- measure only with dosing coup provided
- do not use dosing cup with other products
- dose as follows or as directed by a doctor
- Adults and children 12 years and older: 20 mL in dosing cup provided every 4 hours
- Children under 12 years of age: Do not use

Other information

- each 20 mL contains: sodium 20 mg
- store between 15-30oC(59-86oF)
- do not refrigerate
- dosing cup provided

Inactive ingredients

citric acid anhydrous, edetate disodium, FDand C blue 1, FD and C red 40, flavors, glycerin, propylene glycol, propyl gallate, purified water, sodium benzoate, sodium citrate, sorbitol, sucralose, xanthan gum

PDP

compare to the active ingredients in Mucinex Fast Max Severe Cough and congestion

Maximum strength Tussnex FM

Severe Cough and Congestion

Dextromethorphan HBr

Cough Suppressant

Guaifenesin

Expectorant

Phenylephrine HCl

Nasal Decongestant

Relieves:

Soothes cough

Thins and loosens mucus

Relieves Nasal and chest congestion

For ages 12 and over